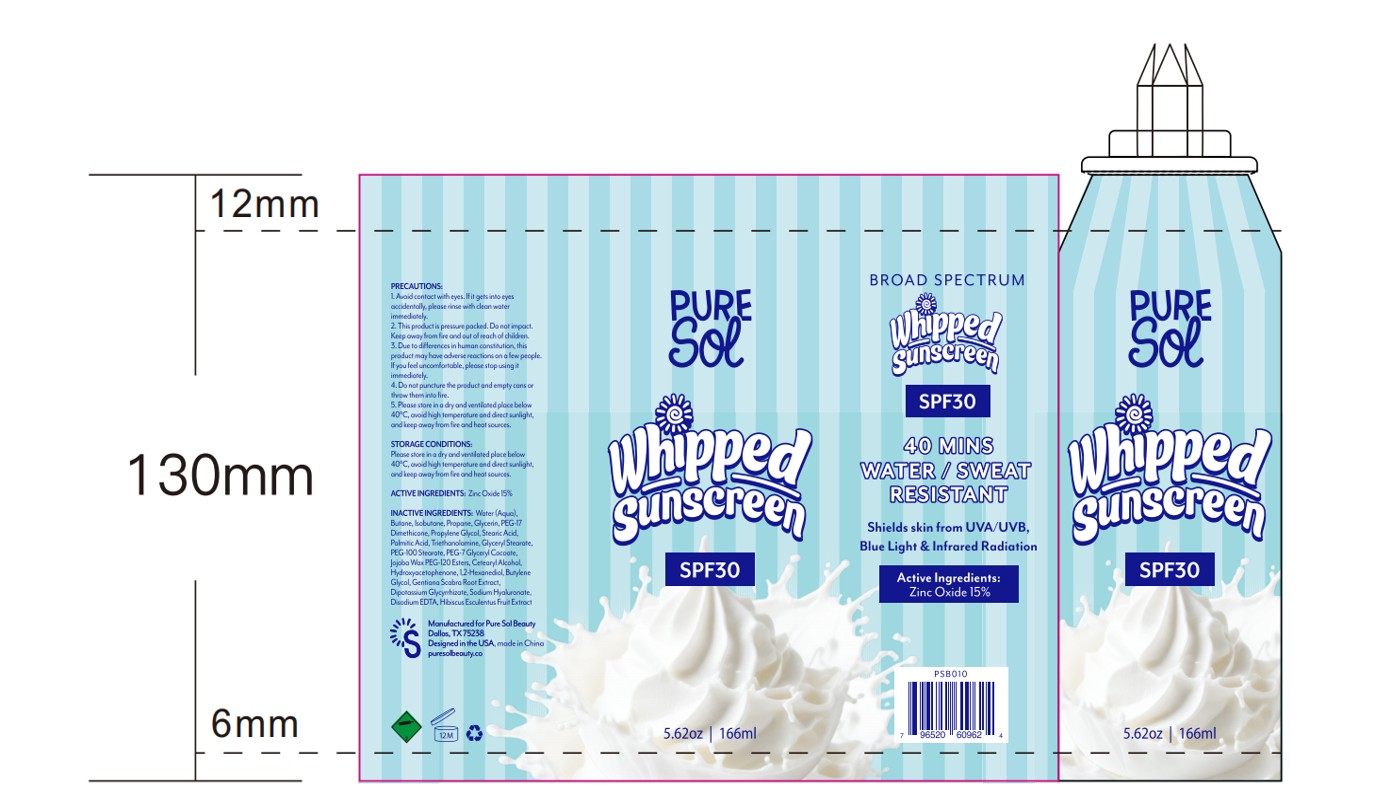 DRUG LABEL: PURE SOL SPF 30 Mineral Whipped Sunscreen
NDC: 84090-003 | Form: SPRAY
Manufacturer: Brand 2022b LLC
Category: otc | Type: HUMAN OTC DRUG LABEL
Date: 20251004

ACTIVE INGREDIENTS: ZINC OXIDE 15 g/100 mL
INACTIVE INGREDIENTS: PROPANE; STEARIC ACID; PEG-7 GLYCERYL COCOATE; WATER; GENTIANA SCABRA ROOT; PROPYLENE GLYCOL; CETEARYL ALCOHOL; TRIETHANOLAMINE; HYDROXYACETOPHENONE; BUTYLENE GLYCOL; GLYCERYL STEARATE; EDETATE DISODIUM; PEG-12 DIMETHICONE; PALMITIC ACID; PEG-100 STEARATE; DIPOTASSIUM GLYCYRRHIZATE; HYDROGENATED JOJOBA OIL/JOJOBA OIL, RANDOMIZED (IODINE VALUE 64-70); 1,2-HEXANEDIOL; ISOBUTANE; BUTANE; GLYCERIN; SODIUM HYALURONATE; OKRA

84090-003-01.PURE SOL SPF 30 Mineral Whipped Sunscreen- Spray-166ml

ACTIVE INGREDIENT

Zinc Oxide（nano） 15%

Keep out of reach of children.

If swallowed, get medical help or contact a
Poison Control Center immediately.

PURPOSE

• helps prevent sunburn • higher SPF gives more sunburn protection
• helps protect the skin against the harmful effects of UVA and UVB rays

WARNINGS

For external use only

When using this product

• Avoid contact with the eyes. If contact occurs
rinse thoroughly with water
• do not puncture or incinerate. Contents under pressure. Do not store at
temperatures above 120°F

INDICATIONS AND USAGE

• apply generously and evenly to all exposed areas before sun exposure
• reapply as needed or after towel drying, swimming, perspiring or vigorous
activity • children under 6 months of age: ask a doctor
• do not spray directly on face. Spray into hands and apply to face
• use in well-ventilated areas

INACTIVE INGREDIENT

Water
Butane
Isobutane
Propane
Glycerin
PEG-17 Dimethicone
Propylene Glycol
Stearic Acid
Palmitic Acid
Triethanolamine
Glyceryl Stearate
PEG-100 Stearate
PEG-7 Glyceryl Cocoate
Jojoba Wax PEG-120 Esters
Cetearyl Alcohol
Hydroxyacetophenone
1,2-Hexanediol
Butylene Glycol
Gentiana Scabra Root Extract
Dipotassium Glycyrrhizate
Sodium Hyaluronate
Disodium EDTA
Hibiscus Esculentus Fruit Extract

DOSAGE AND ADMINISTRATION

Apply tiberally 15 minutes before sun exposure.
Reapoly. at least every 2 hours or after 80 minutes of swimming or sweating.